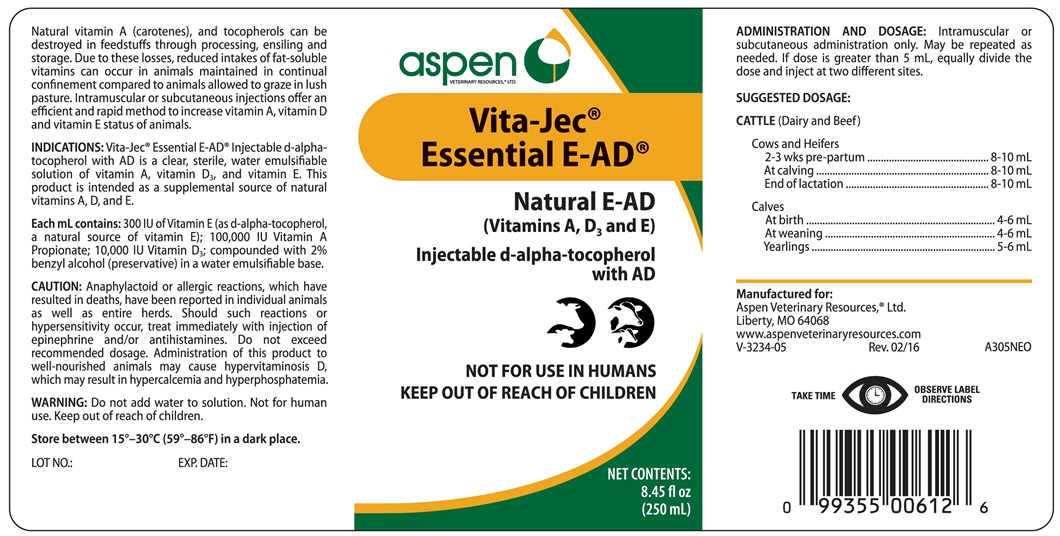 DRUG LABEL: Vita-Jec Essential E-AD
NDC: 46066-239 | Form: INJECTION
Manufacturer: Aspen Veterinary Resources, Ltd.
Category: animal | Type: OTC ANIMAL DRUG LABEL
Date: 20180223

ACTIVE INGREDIENTS: .ALPHA.-TOCOPHEROL, D- 201 mg/1 mL; VITAMIN A 3.6 mg/1 mL; VITAMIN D 2.5 mg/1 mL

Vita-Jec Essential E-AD

INDICATIONS AND USAGE

NATURAL E-AD

(Vitamin A, D3, and E)

Injectable d-alpha-tocopherol with AD

NOT FOR USE IN HUMANS

KEEP OUT OF REACH OF CHILDREN

Natural vitamin A (carotenes), and tocopherols can be destroyed in feedstuffs through processing, ensiling and storage. Due to these losses, reduced intakes of fat-soluble vitamins can occur in animals maintained in continual confinement compared to animals allowed to graze in lush pasture. Intramuscular or subcutaneous injections offer an efficient and rapid method to increase vitamin A, vitamin D and Vitamin E status of animals.

INDICATIONS

Vita-Jec Essential E-AD Injectable d-alpha-tocopherol with AD is clear, sterile, water emulsifiable solution of vitamin A, Vitamin D3, and vitamin E. This product is intended as a supplemental source of natural vitamins A, D, and E.

Each mL contains:

300 IU of Vitamin E (as d-alpha-tocopherol, a natural source of vitamin E); 100,000 IU Vitamin A Propionate; 10,000 IU Vitamin D3; compunded with 2% benzyl alcohol (preservative) in a water emulsifiable base.

CAUTION

Anaphylactoid or allergic reactions, which have resulted in deaths, have been reported in individual animals as well as entire herds. Should such reactions or hypersensitivity occur, treat immediately with injection of epinephrine and/or antihistamines. Do not exceed recommended dosage. Administration of this product to well-nourished animals may cause hypervitaminosis D, which may result in hypercalcemia and hyperphosphatemia.

WARNING

Do not add water to solution. Not for human use. Keep out of reach of children.

STORAGE AND HANDLING

Store between 15° and 30°C (59°-86°F) in a dark place.

TAKE TIME OBSERVE LABEL DIRECTIONS

DOSAGE AND ADMINISTRATION

Intramuscular or subcutaneous administration only. If dose is greater than 5 mL, equally divide the dose and inject at two different sites. May be repeated.

SUGGESTED DOSAGE mL

CATTLE (Diary and Beef)

Cows and Heifers

2-3 wks pre-partum ..................... 6-10

At calving ................................... 8-10

End of lactation ........................... 8-10

Calves

At birth ....................................... 4-6

At weaning .................................. 4-6

Yearlings ..................................... 5-6